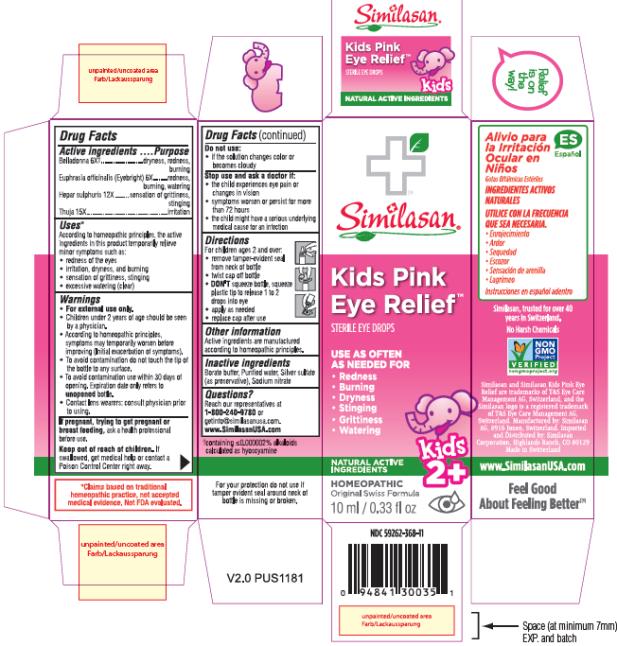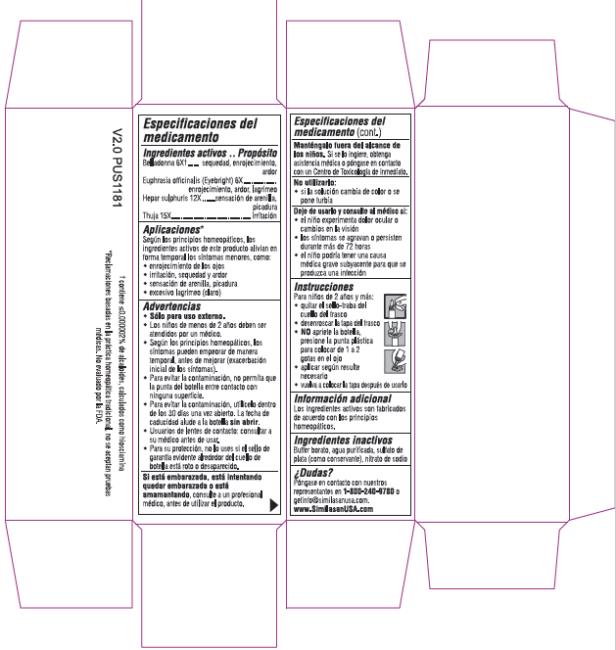 DRUG LABEL: Kids Pink Eye Relief
NDC: 59262-368 | Form: LIQUID
Manufacturer: Similasan Corporation
Category: homeopathic | Type: HUMAN OTC DRUG LABEL
Date: 20220214

ACTIVE INGREDIENTS: ATROPA BELLADONNA 6 [hp_X]/10 mL; EUPHRASIA STRICTA 6 [hp_X]/10 mL; CALCIUM SULFIDE 12 [hp_X]/10 mL; PLATYCLADUS ORIENTALIS LEAF 15 [hp_X]/10 mL
INACTIVE INGREDIENTS: BORIC ACID; WATER; SILVER SULFATE; SODIUM NITRATE

Kids Pink Eye Relief

Drug Facts

Active ingredients

Belladonna 6X†

Euphrasia officinalis (Eyebright) 6X

Hepar sulphuris 12X

Thuja 15X

Purpose

dryness, redness, burning

redness, burning, watering

sensation of grittiness, stinging

irritation

Uses*

According to homeopathic principles, the active ingredients in this product temporarily relieve minor symptoms such as:

• redness of the eyes

• irritation, dryness, and burning

• sensation of grittiness

• excessive watering (clear)

Warnings

• For external use only.

• Children under 2 years of age should be seen by a physician.

• According to homeopathic principles, symptoms may temporarily worsen before improving (Initial exacerbation of symptoms).

• To avoid contamination do not touch the tip of the bottle to any surface.

• To avoid contamination use within 30 days of opening. Expiration date only refers to unopened bottle.

• Contact wearers: consult physician prior to using.

If pregnant, trying to get pregnant or breast feeding,

ask a health professional before use.

Keep out of reach of children.

If swallowed, get medical help or contact a Poison Control Center right away.

Do not use:

• if the solution changes color or becomes cloudy

Stop use and ask a doctor if:

• the child experiences eye pain or changes in vision

• symptoms worsen or persist for more than 72 hours

- the child might have a serious underlying medical cause for an infection

Directions

For children ages 2 and over:

• remove tamper-evident seal from neck of bottle

• twist cap off bottle

• DON'T squeeze bottle, squeeze plastic tip to release 1 to 2 drops into eye

• apply as needed

• replace cap after use

Other information

Active ingredients are manufactured according to homeopathic principles.

Inactive ingredients

Borate buffer, Purified water, Silver sulfate (as preservative), Sodium nitrate

Questions?

Reach our representatives at 1-800-240-9780 or getinfo@similasanusa.com.

www.SimilasanUSA.com

†containing 0.000002% alkaloids calculated as hyoscyamine

PRINCIPAL DISPLAY PANEL

NDC 59262-368-11
Similasan
Kids
Pink Eye
Relief
STERILE EYE DROPS
10 ml / 0.33 fl oz